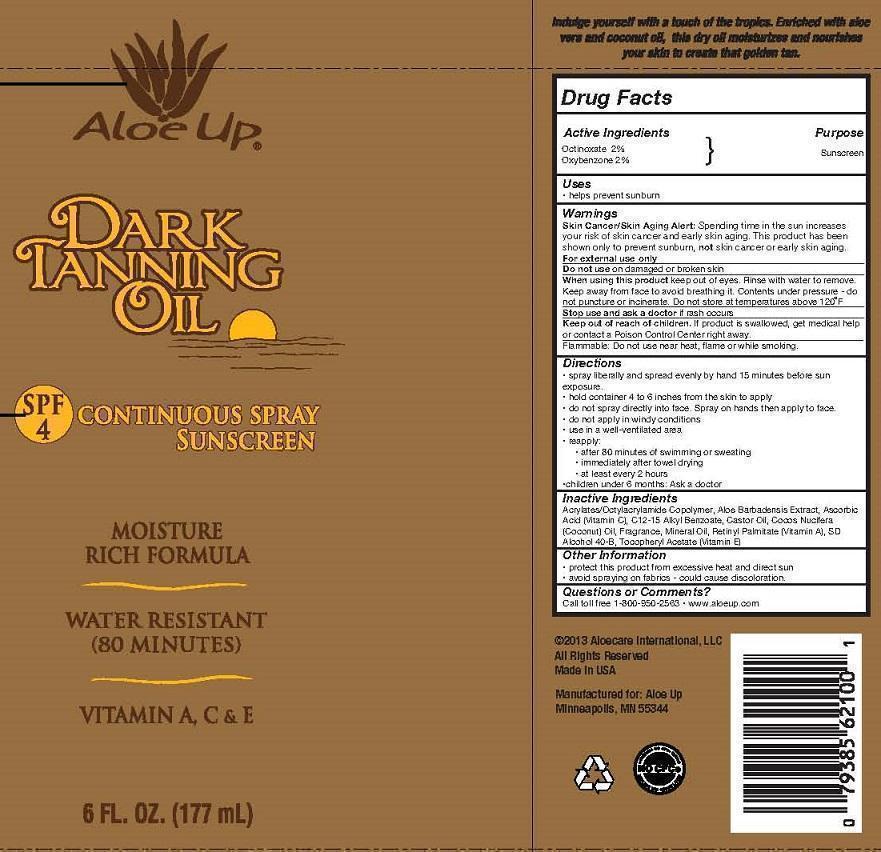 DRUG LABEL: ALOE UP DARK TANNING OIL SPF 4
NDC: 61477-216 | Form: SPRAY
Manufacturer: Aloe Care International, LLC
Category: otc | Type: HUMAN OTC DRUG LABEL
Date: 20240213

ACTIVE INGREDIENTS: OXYBENZONE 2 g/100 mL; OCTINOXATE 2 g/100 mL
INACTIVE INGREDIENTS: ASCORBIC ACID; ALKYL (C12-15) BENZOATE; CASTOR OIL; ALOE VERA LEAF; COCONUT OIL; MINERAL OIL; VITAMIN A PALMITATE; ALCOHOL; .ALPHA.-TOCOPHEROL ACETATE; CARBOMER HOMOPOLYMER TYPE B (ALLYL SUCROSE CROSSLINKED)

ALOE UP - SPF 4 TANNING OIL SPRAY (61477-216)

ACTIVE INGREDIENTS:

OCTINOXATE (2%)

OXYBENZONE (2%)

PURPOSE:

SUNSCREEN

USES

HELPS PREVENT SUNBURN.

DIRECTIONS:

• spray liberally and spread evenly by hand 15 minutes before sun exposure.
• hold container 4 to 6 inches from the skin to apply
• do not spray directly into face. Spray on hands then apply to face.
• do not apply in windy conditions
• use in a well-ventilated area
• reapply:
• after 80 minutes of swimming or sweating
• immediately after towel drying
• at least every 2 hours
•children under 6 months: Ask a doctor

Keep out of reach of children. If product is swallowed, get medical help or contact a Poison Control Center right away.

WARNINGS:

Skin Cancer/Skin Aging Alert: Spending time in the sun increases your risk of skin cancer and early skin aging. This product has been shown only to prevent sunburn, not skin cancer or early skin aging.
For external use only.
Do not use on damaged or broken skin.
When using this product keep out of eyes. Rinse with water to remove.
Keep away from face to avoid breathing it. Contents under pressure - do not puncture or incinerate. Do not store at temperatures above 120°F.
Stop use and ask a doctor if rash occurs.
Flammable: Do not use near heat, flame or while smoking.

Inactive Ingredients

Acrylates/Octylacrylamide Copolymer, Aloe Barbadensis Extract, Ascorbic Acid (Vitamin C), C12-15 Alkyl Benzoate, Castor Oil, Cocos Nucifera (Coconut) Oil, Fragrance, Mineral Oil, Retinyl Palmitate (Vitamin A), SD Alcohol 40-B, Tocopheryl Acetate (Vitamin E)

Other Information

• protect this product from excessive heat and direct sun
• avoid spraying on fabrics - could cause discoloration.

Questions or Comments?

Call toll free 1-800-950-2563 • www.aloeup.com